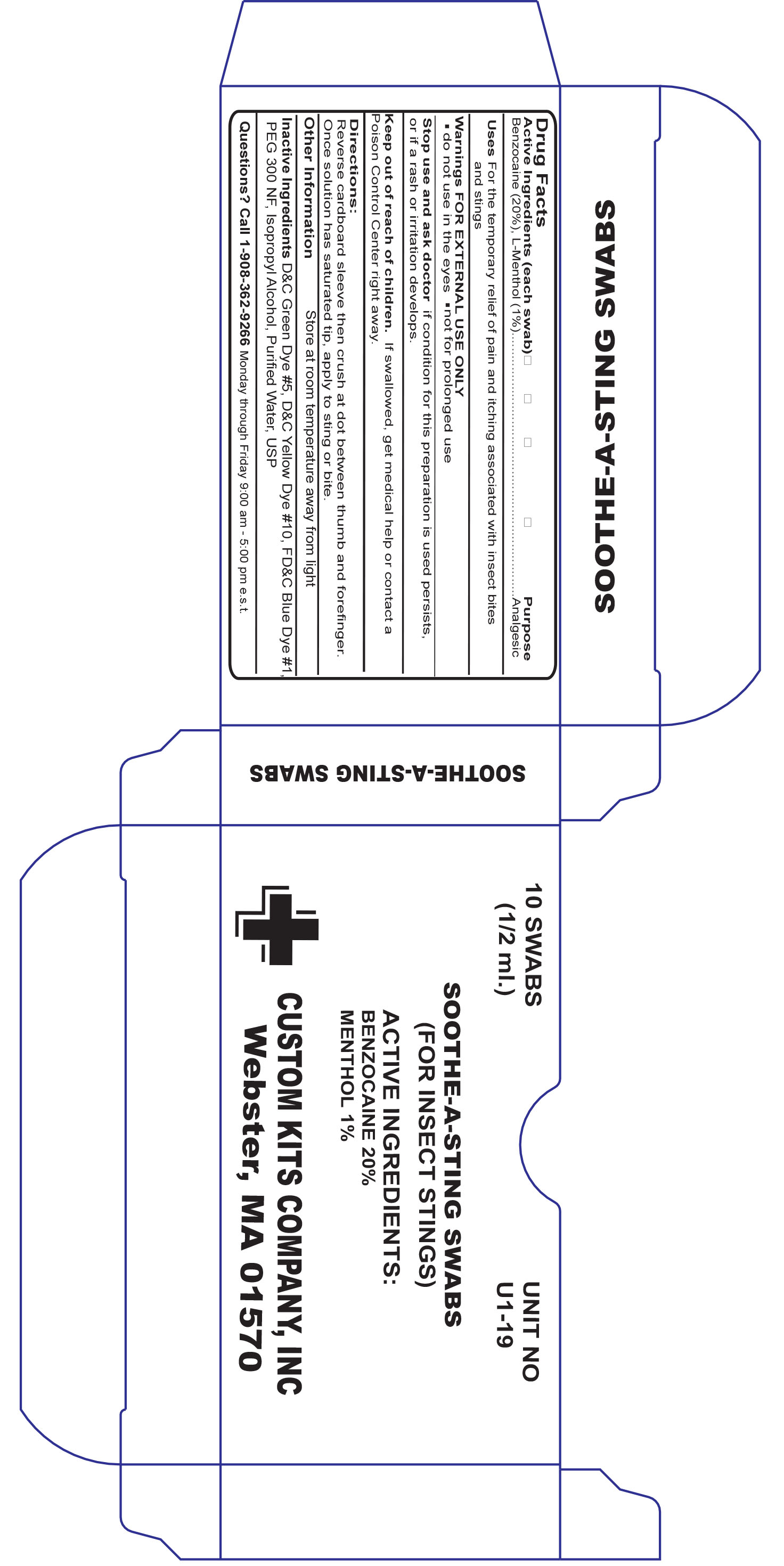 DRUG LABEL: Medicaine Sting and Bite
NDC: 68183-118 | Form: SWAB
Manufacturer: Custom Kits Company Inc
Category: otc | Type: HUMAN OTC DRUG LABEL
Date: 20200117

ACTIVE INGREDIENTS: BENZOCAINE 0.12 g/1 g
INACTIVE INGREDIENTS: WATER

Medicane Sting and Bite

Active ingredient

Benzocaine (20%), L-Methol (1%)

PURPOSE

analgesic

Uses

For temporary relief of pain and itching associated with insect bites and stings

Warning

Do not use in the eyes

Not for prolonged use

Stop use

If condition for this preparatiob is used persists or if a rash or irritation develops

Keep out of reach of children

If swallowed, get medical help or contact a poison control center right away

Directions

reverse cardboard sleeve then crish at dot between thumb and forefinger. Once solution has saturated tip, apply to sting or bite.

Other Safety Information

Store at room temperature away from light

Inactive Ingredients

D&C Green Dye #5 D&C Yellow Dye #10, FD&C Blue Dye #1, PEG 300 NF, Isopropyl Alcohol, Purified Water, USP